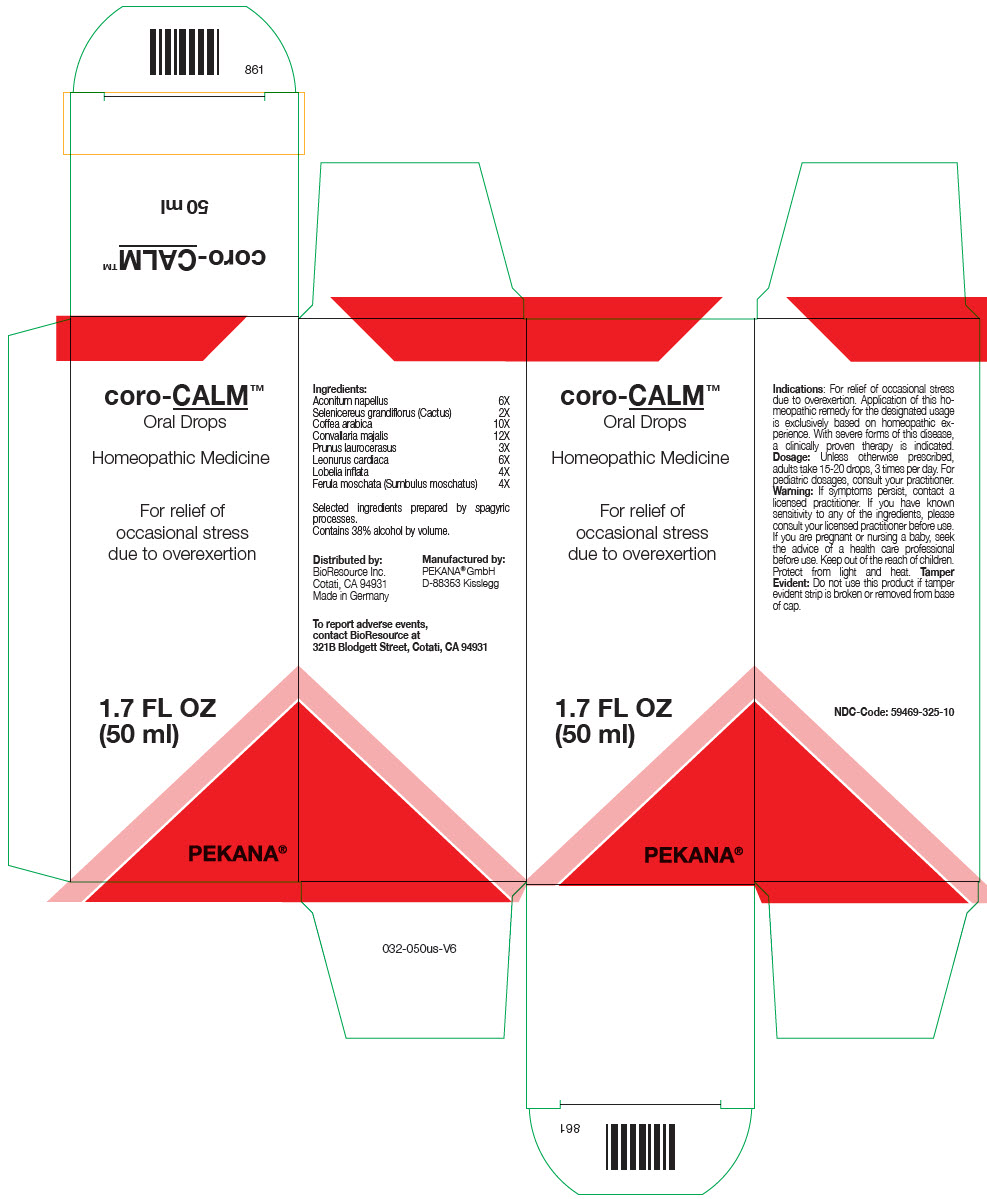 DRUG LABEL: coro-CALM
NDC: 59469-325 | Form: SOLUTION/ DROPS
Manufacturer: PEKANA Naturheilmittel GmbH
Category: homeopathic | Type: HUMAN OTC DRUG LABEL
Date: 20230111

ACTIVE INGREDIENTS: ACONITUM NAPELLUS WHOLE 6 [hp_X]/50 mL; SELENICEREUS GRANDIFLORUS WHOLE 2 [hp_X]/50 mL; ARABICA COFFEE BEAN 10 [hp_X]/50 mL; LOBELIA INFLATA WHOLE 4 [hp_X]/50 mL; FERULA SUMBUL ROOT 4 [hp_X]/50 mL; CONVALLARIA MAJALIS FLOWERING TOP 12 [hp_X]/50 mL; PRUNUS LAUROCERASUS LEAF 3 [hp_X]/50 mL; LEONURUS CARDIACA FLOWERING TOP 6 [hp_X]/50 mL
INACTIVE INGREDIENTS: WATER; ALCOHOL

coro-CALM™

ACTIVE INGREDIENT

Ingredients:
Aconitum napellus | 6X
Selenicereus grandiflorus (Cactus) | 2X
Coffea arabica | 10X
Convallaria majalis | 12X
Prunus laurocerasus | 3X
Leonurus cardiaca | 6X
Lobelia inflata | 4X
Ferula moschata (Sumbulus moschatus) | 4X

Selected ingredients prepared by spagyric processes.

INACTIVE INGREDIENT

Contains 38% alcohol by volume.

Indications

PURPOSE

For relief of occasional stress due to overexertion. Application of this homeopathic remedy for the designated usage is exclusively based on homeopathic experience. With severe forms of this disease, a clinically proven therapy is indicated.

Dosage

Unless otherwise prescribed, adults take 15-20 drops, 3 times per day. For pediatric dosages, consult your practitioner.

Warning

If symptoms persist, contact a licensed practitioner. If you have known sensitivity to any of the ingredients, please consult your licensed practitioner before use. If you are pregnant or nursing a baby, seek the advice of a health care professional before use.

Keep out of the reach of children.

STORAGE AND HANDLING

Protect from light and heat.

Tamper Evident

Do not use this product if tamper evident strip is broken or removed from base of cap. Oral Drops Homeopathic Medicine For relief of occasional stress due to overexertion

QUESTIONS

To report adverse events, contact BioResource at 321B Blodgett Street, Cotati, CA 94931

Distributed by:
BioResource Inc.
Cotati, CA 94931

Manufactured by:
PEKANA® GmbH
D-88353 Kisslegg

PRINCIPAL DISPLAY PANEL - 50 ml Bottle Box

coro-CALM™

Oral Drops

Homeopathic Medicine

For relief of
occasional stress
due to overexertion

1.7 FL OZ
(50 ml)

PEKANA®